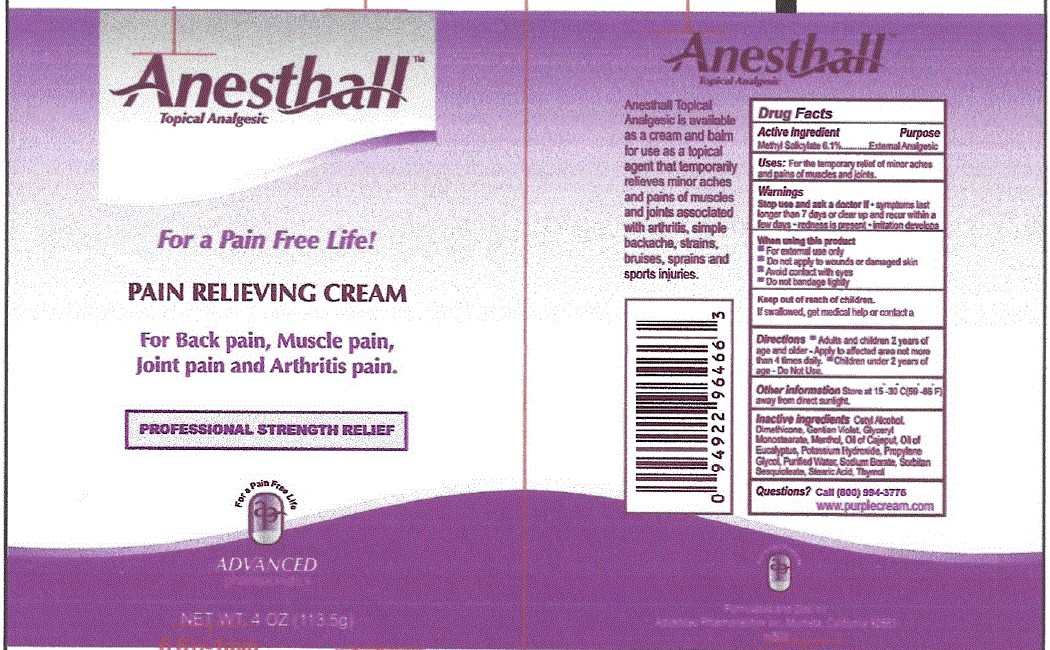 DRUG LABEL: Anesthall Pain Relieving Cream
NDC: 84006-101 | Form: CREAM
Manufacturer: Advanced Pharmaceutics Inc
Category: otc | Type: HUMAN OTC DRUG LABEL
Date: 20240111

ACTIVE INGREDIENTS: METHYL SALICYLATE 6.1 g/100 g; MENTHOL 4.6 g/100 g
INACTIVE INGREDIENTS: SILICON; GENTIAN VIOLET; SODIUM BORATE; PROPYLENE GLYCOL; WATER; POTASSIUM HYDROXIDE; SORBITAN SESQUIOLEATE; CETYL ALCOHOL; GLYCERYL MONOSTEARATE; METHYL GLUCOSE DIOLEATE; STEARIC ACID; THYMOL; EUCALYPTUS OIL; MELALEUCA VIRIDIFLORA FLOWERING TOP

Active ingredients

Menthol USP 12%

Camphor 6%

Purpose

Methyl Salicylate 6.1%..................... External Analgesic

Menthol 4.6%....................................External Analgesic

Uses

for temporary relief of minor aches and pains of muscles and joints associated with:

- simple backache
- arthritis
- strains
- bruises
- Sprains

Warnings

For external use only

Do not use

- on damaged or broken skin

When using this product

- do not bandage tightly
- avoid contact with eyes

Stop use and ask doctor if

- condition worses or if symptoms persist for more than 7 days, or clear up and occur again within a few days
- redness is present
- irritation develops

Keep out of reach of children. If swallowed, get medical help or contact a Poison Control Center immediately.

Directions

- Adults and children 2 years of age and older:Apply to affected area not more than 4 times daily
- Children under 2 years of age: Do Not Use

Other information

- Store at 15-30C (59-86F) away from direct sunlight

Inactive ingredients

Cetyl Alcohol, Dimethicone, Gentian Violet, Glyceryl Monostearate, Oil of Cajeput, Oil of Eucalyptus, Potassium Hydroxide, Propylene Glycol, Water, Sodium Borate, Sorbitan Sesquioleate, Stearic Acid, Thymol.

PACKAGE LABEL

Anesthall

Pain Relieving Cream

Methyl Salicylate 6.1%

Menthol 4.6%

For temporary relief of minor aches and pains

Net Wt. 4 oz (113.5 g)